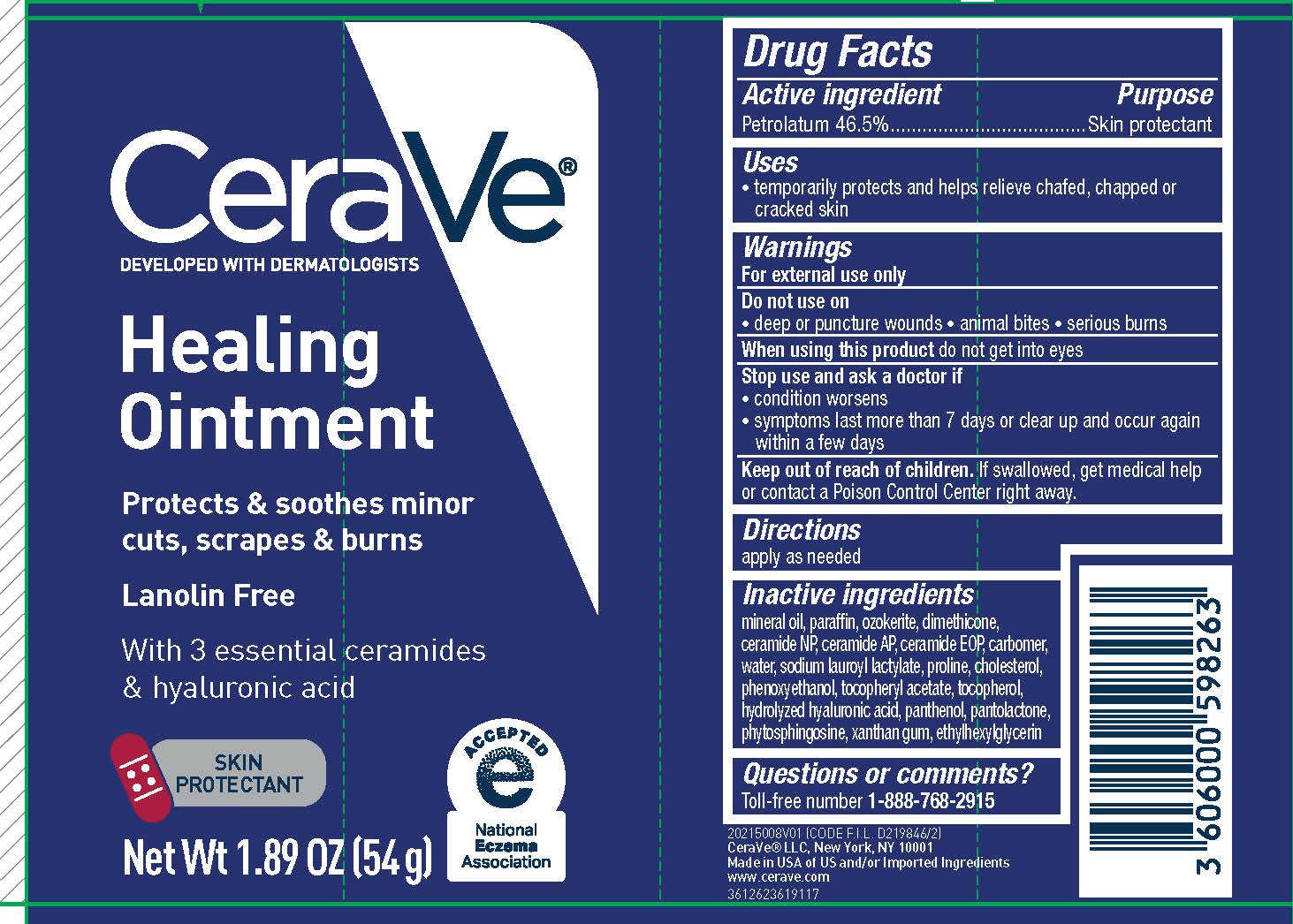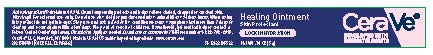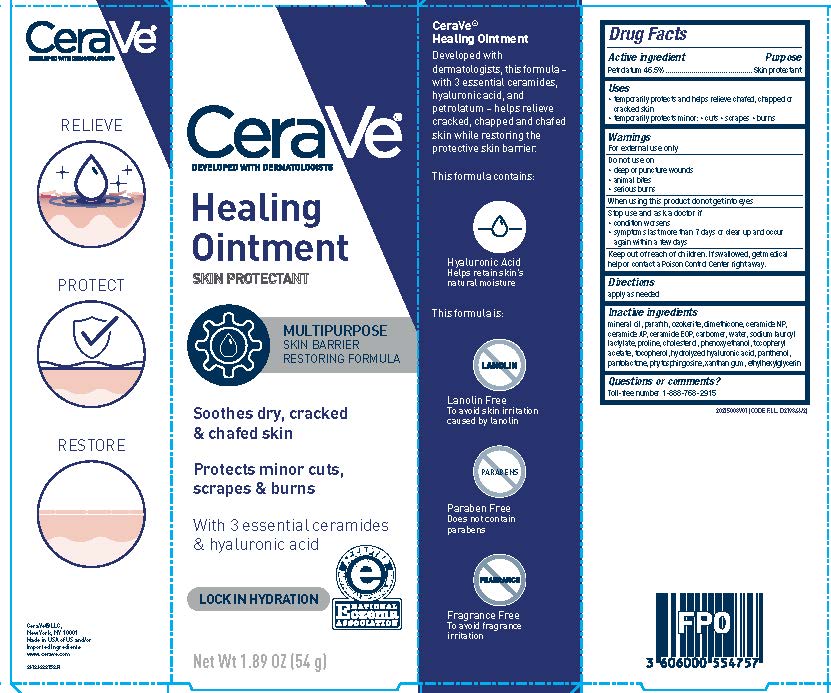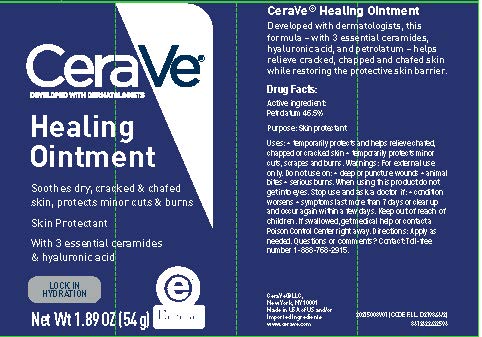 DRUG LABEL: CeraVe Developed with Dermatologists Healing
NDC: 49967-500 | Form: OINTMENT
Manufacturer: L'Oreal USA Products Inc.
Category: otc | Type: HUMAN OTC DRUG LABEL
Date: 20231231

ACTIVE INGREDIENTS: PETROLATUM 46.5 g/100 g
INACTIVE INGREDIENTS: MINERAL OIL; PARAFFIN; CERESIN; DIMETHICONE; CERAMIDE 1; CERAMIDE 3; CERAMIDE 6 II; CARBOMER HOMOPOLYMER, UNSPECIFIED TYPE; WATER; SODIUM LAUROYL LACTYLATE; LAUROYL PROLINE; CHOLESTEROL; PHENOXYETHANOL; .ALPHA.-TOCOPHEROL ACETATE; TOCOPHEROL; HYALURONIC ACID; PANTHENOL; PANTOLACTONE; PHYTOSPHINGOSINE; XANTHAN GUM; ETHYLHEXYLGLYCERIN

Drug Facts

Active ingredient

Petrolatum 46.5%

Purpose

Skin protectant

Uses

• temporarily protects and helps relieve chafed, chapped or cracked skin

- temporarily protects minor: ● cuts ● scrapes ● burns
- helps protect from the drying effects of wind and cold weather

Warnings

For external use only

Do not use on

- deep or puncture wounds
- animal bites
- serious burns

When using this product

do not get into eyes

Stop use and ask a doctor if

- condition worsens
- symptoms last more than 7 days or clear up and occur again within a few days

Keep out of reach of children.

If swallowed, get medical help or contact a Poison Control Center immediately.

Directions

apply as needed

Inactive ingredients

mineral oil, paraffin, ozokerite, dimethicone, ceramide NP, ceramide AP, ceramide EOP, carbomer, water, sodium lauroyl lactylate, proline, cholesterol, phenoxyethanol, tocopheryl acetate, tocopherol, hydrolyzed hyaluronic acid, panthenol, pantolactone, phytosphingosine, xanthan gum, ethylhexylglycerin

Questions?

Toll-Free Number 1-888-768-2915

www.cerave.com